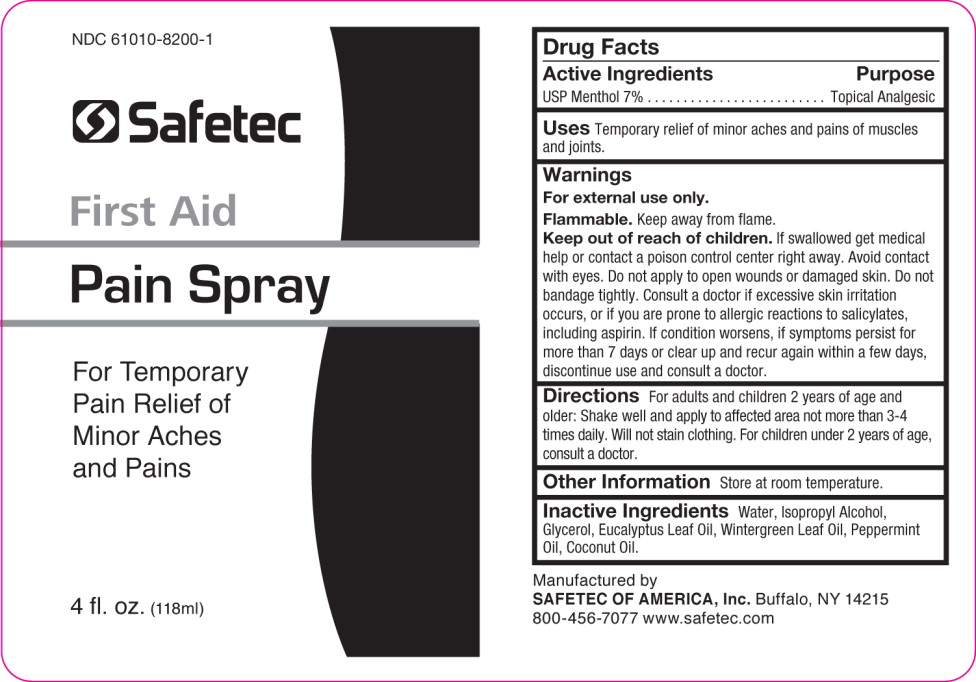 DRUG LABEL: Analgesic
NDC: 61010-8200 | Form: SPRAY
Manufacturer: Safetec of America, Inc.
Category: otc | Type: HUMAN OTC DRUG LABEL
Date: 20240302

ACTIVE INGREDIENTS: MENTHOL, UNSPECIFIED FORM 70 mg/1 mL
INACTIVE INGREDIENTS: WATER; ISOPROPYL ALCOHOL; GLYCERIN; EUCALYPTUS OIL; METHYL SALICYLATE; PEPPERMINT OIL; COCONUT OIL

61010-8200, PAIN SPRAY

Pain Spray

Drug Facts

Active Ingredients

USP Menthol 7%

Purpose

Topical Analgesic

Uses:

For the temporary relief of minor aches and pains of muscles and joints.

Warnings:

- For external use only
- Flammable.Keep away from flame.

- Keep out of reach of children-if swallowed get medical help or contact a poison center right away. Avoid contact with eyes. Do not apply to open wounds or damaged skin. Do not bandage tightly. Consult a doctor if excessive skin irritation occurs, or if you are prone to allergic reactions to salicylates, including aspirin. If condition worsens, if symptoms persist for more than 7 days or clear up and recur again within a few days, discontinue use of this product and consult a doctor.

Directions:

For adults and children 2 years of age and older: Shake well and apply to affected area not more than 3-4 times daily. Will not stain clothing. For children under 2 years of age, consult a doctor.

Other Information:

Store at room temperature.

Inactive Ingredients:

Water, Isopropyl Alcohol, Glycerol, Eucalyptus Leaf Oil, Wintergreen Leaf Oil, Peppermint Oil, Coconut Oil.

Manufactured by
SAFETEC OF AMERICA, Inc. Buffalo, NY 14215
800-456-7077 www.safetec.com

PRINCIPAL DISPLAY PANEL

NDC 61010-8200-1

Safetec

First Aid

Pain Spray

For Temporary

Pain Relief of

Minor Aches

And Pains

4 fl. oz. (118 ml)